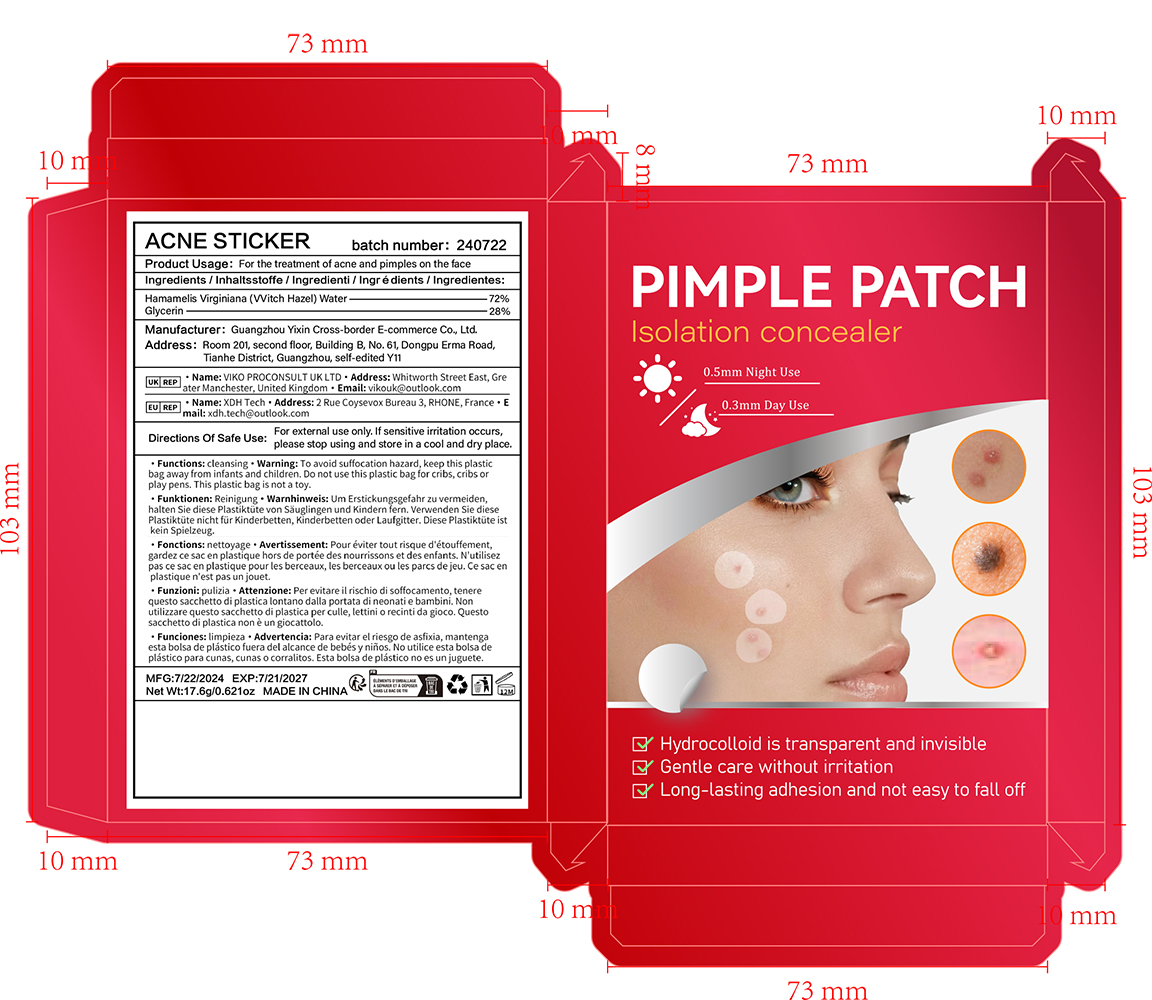 DRUG LABEL: ACNE STICKER
NDC: 84372-015 | Form: PATCH
Manufacturer: Shenzhen Zhumeng Times Technology Co., Ltd.
Category: otc | Type: HUMAN OTC DRUG LABEL
Date: 20240821

ACTIVE INGREDIENTS: HAMAMELIS VIRGINIANA TOP WATER 7.2 g/100 g
INACTIVE INGREDIENTS: GLYCERIN

Active ingredients

Hamamelis Virginiana (Vvitch Hazel) Water-72%

Purpose

For the treatment of acne and pimples on the face

Uses

Clean your skin first, choose a suitable size and stick it on the acne, wait for a few hours, and then wash it with warm water

Warnings

For external use only.

If sensitive irritation occurs, please stop using and store in a cool and dry place.

Dosage and administration

For external use only.

Do not use

Please make sure your skin is clean before use. Avoid using on open wounds or skin with allergic reactions.

When using section

Clean the skin with warm water to ensure that the skin surface is clean. Choose the appropriate size of acne patch that can completely cover the acne. Let the acne patch stay on the skin for a sufficient time. After the use time is over, you can clean the skin with warm water.

stop use

Do not use on open wounds or allergic skin.

Keep out of reach of children.

If sxralowed, get medical help or contact a Poison Conirol Cenler ngiht away.

Inactive ingredients

Glycerin